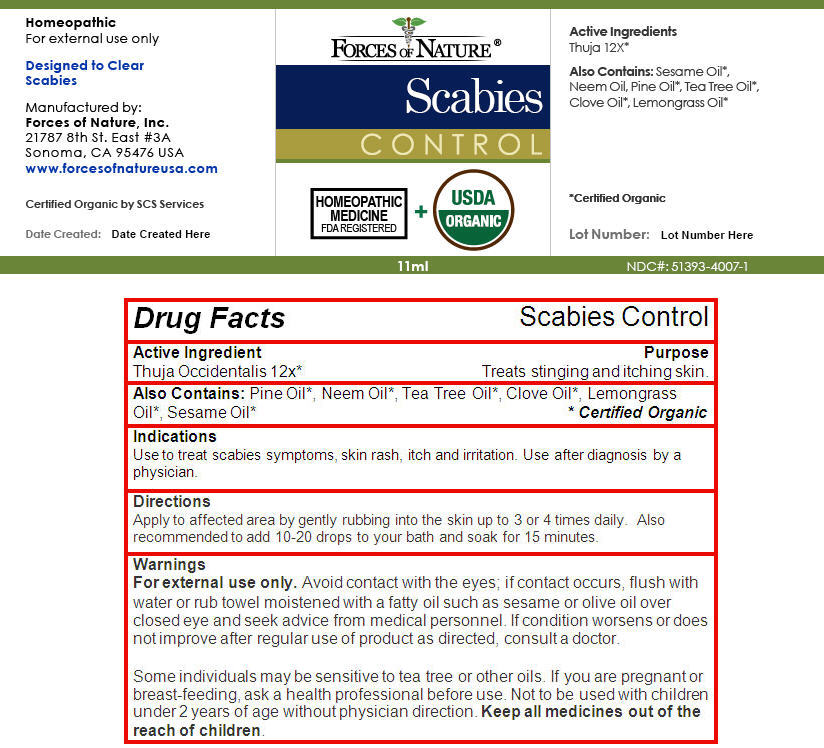 DRUG LABEL: Scabies Control
NDC: 51393-4007 | Form: SOLUTION/ DROPS
Manufacturer: Forces of Nature
Category: homeopathic | Type: HUMAN OTC DRUG LABEL
Date: 20131217

ACTIVE INGREDIENTS: THUJA OCCIDENTALIS LEAF 12 [hp_X]/100 mL
INACTIVE INGREDIENTS: PINE NEEDLE OIL (PINUS SYLVESTRIS); AZADIRACHTA INDICA SEED OIL; TEA TREE OIL; CLOVE OIL; WEST INDIAN LEMONGRASS OIL; SESAME OIL

Scabies Control

Drug Facts

Active Ingredient

Thuja Occidentalis 12x [Certified Organic]

Purpose

Treats stinging and itching skin.

Also Contains

Pine Oil, Neem Oil, Tea Tree Oil, Clove Oil, Lemongrass Oil, Sesame Oil

Indications

Use to treat scabies symptoms, skin rash, itch and irritation. Use after diagnosis by a physician.

Directions

Apply to affected area by gently rubbing into the skin up to 3 or 4 times daily. Also recommended to add 10-20 drops to your bath and soak for 15 minutes.

Warnings

WHEN USING

For external use only. Avoid contact with the eyes; if contact occurs, flush with water or rub towel moistened with a fatty oil such as sesame or olive oil over closed eye and seek advice from medical personnel.

ASK DOCTOR

If condition worsens or does not improve after regular use of product as directed, consult a doctor.

Some individuals may be sensitive to tea tree or other oils.

PREGNANCY OR BREAST FEEDING

If you are pregnant or breast-feeding, ask a health professional before use.

KEEP OUT OF REACH OF CHILDREN

Not to be used with children under 2 years of age without physician direction. Keep all medicines out of the reach of children.

Manufactured by:
Forces of Nature, Inc.
21787 8th St. East #3A
Sonoma, CA 95476 USA

PRINCIPAL DISPLAY PANEL - 11 ml Bottle Label

FORCES OF NATURE ®

Scabies

CONTROL

HOMEOPATHIC
MEDICINE
FDA REGISTERED

+

USDA
ORGANIC

11ml